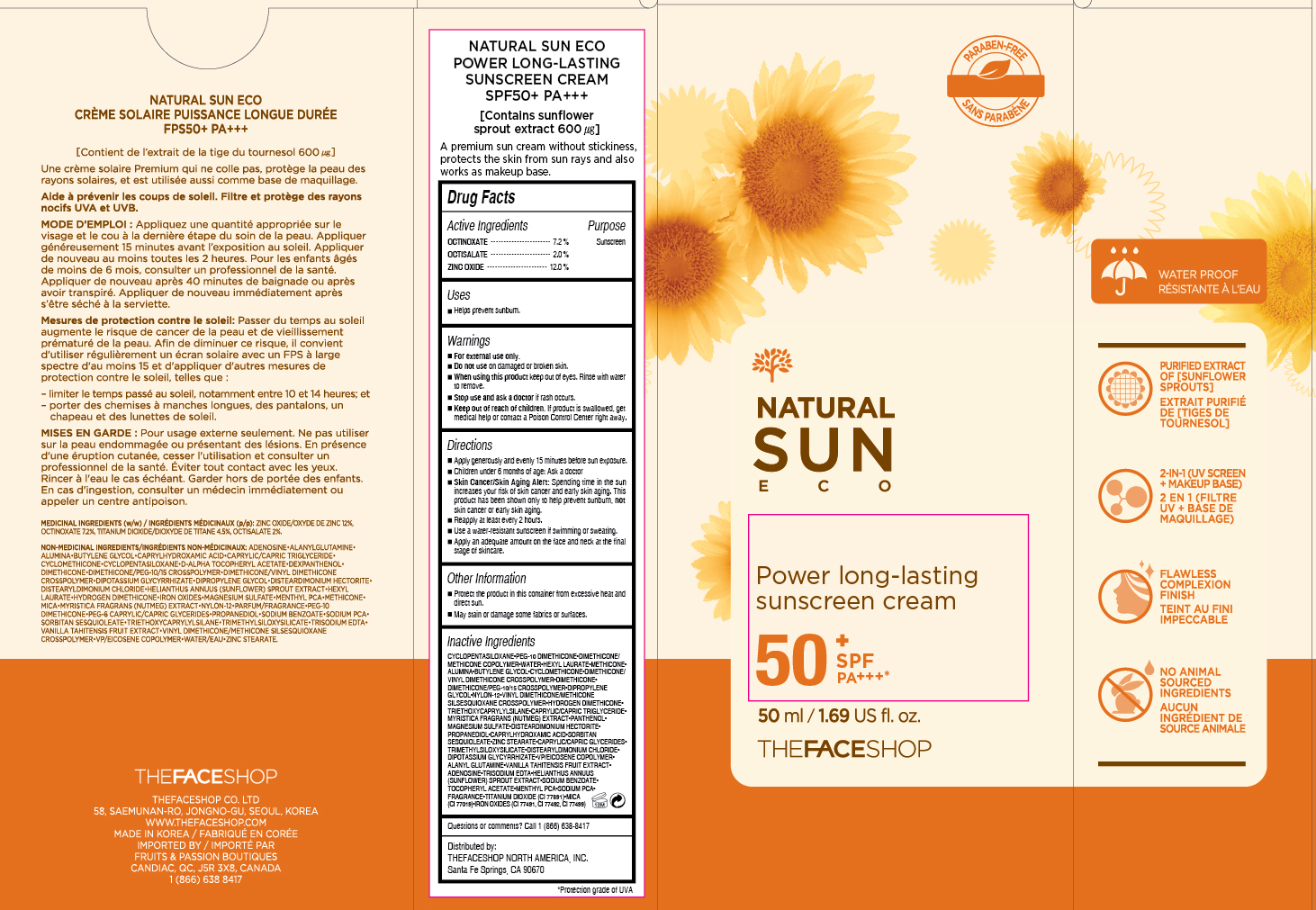 DRUG LABEL: NATURAL SUN ECO
NDC: 51523-194 | Form: CREAM
Manufacturer: THEFACESHOP CO., LTD.
Category: otc | Type: HUMAN OTC DRUG LABEL
Date: 20151002

ACTIVE INGREDIENTS: ZINC OXIDE 6 g/50 mL; OCTISALATE 1 g/50 mL; OCTINOXATE 3.6 g/50 mL
INACTIVE INGREDIENTS: WATER

NATURAL SUN ECO Power Long-last SPF50+ PA+++ 31500194

Active Ingredients

Octinoxate 7.2 %
Octisalate 2.0 %
Zinc Oxide 12.0 %

Purpose

Sunscreen
Sunscreen
Sunscreen

Uses

Helps prevent sunburn.

Warnings

For external use only.

Do not use on damaged or broken skin

When using this product keep out of eyes. Rinse with water to remove.

Stop use and ask a doctor if rash occurs.

Keep out of reach of children. If product is swallowed, get medical help or contact a Poison Control Center right away.

Directions

Apply generously and evenly 15 minutes before sun exposure.
Children under 6 months of age: Ask a doctor.
Skin Cancer/Skin Aging Alert: Spending time in the sun increases your risk of skin cancer and early skin aging. This product has been shown only to help prevent sunburn, not skin cancer or early skin aging.
Reapply at least every 2 hours.
Use a water-resistant sunscreen if swimming or sweating.

Apply an adequate amount on the face and neck at the final stage of skincare.

OTHER SAFETY INFORMATION

Protect the product in this container from excessive heat and direct sun.

May stain or damage some fabrics or surfaces.

Inactive Ingredients

CYCLOPENTASILOXANE, PEG-10 DIMETHICONE, DIMETHICONE/METHICONE COPOLYMER, WATER, HEXYL LAURATE, METHICONE, ALUMINA, BUTYLENE GLYCOL, CYCLOMETHICONE, DIMETHICONE/VINYL DIMETHICONE CROSSPOLYMER, DIMETHICONE, DIMETHICONE/PEG-10/15 CROSSPOLYMER, DIPROPYLENE GLYCOL, NYLON-12, VINYL DIMETHICONE/METHICONE SILSESQUIOXANE CROSSPOLYMER, HYDROGEN DIMETHICONE, TRIETHOXYCAPRYLYLSILANE, CAPRYLIC/CAPRIC TRIGLYCERIDE, MYRISTICA FRAGRANS (NUTMEG) EXTRACT, PANTHENOL, MAGNESIUM SULFATE, DISTEARDIMONIUM HECTORITE, PROPANEDIOL, CAPRYLHYDROXAMIC ACID, SORBITAN SESQUIOLEATE, ZINC STEARATE, CAPRYLIC/CAPRIC GLYCERIDES, TRIMETHYLSILOXYSILICATE, DISTEARYLDIMONIUM CHLORIDE, DIPOTASSIUM GLYCYRRHIZATE, VP/EICOSENE COPOLYMER, ALANYL GLUTAMINE, VANILLA TAHITENSIS FRUIT EXTRACT, ADENOSINE, TRISODIUM EDTA, HELIANTHUS ANNUUS (SUNFLOWER) SPROUT EXTRACT, SODIUM BENZOATE, TOCOPHERYL ACETATE, MENTHYL PCA, SODIUM PCA, FRAGRANCE, TITANIUM DIOXIDE (CI 77891), MICA (CI 77019), IRON OXIDES (CI 77491, CI 77492, CI 77499)

Questions or comments? Call 1-866-638-8417

Distributed by:

THEFACESHOP NORTH AMERICA, INC.

Santa Fe Springs, CA 90670

PACKAGE LABEL

NATURAL SUN ECO

Power Long-lasting Sunscreen Cream

SPF 50+

Contains sunflower sprout extract 600 µg

A premium sun cream without stickiness, protects the skin from sun rays and also works as makeup base.